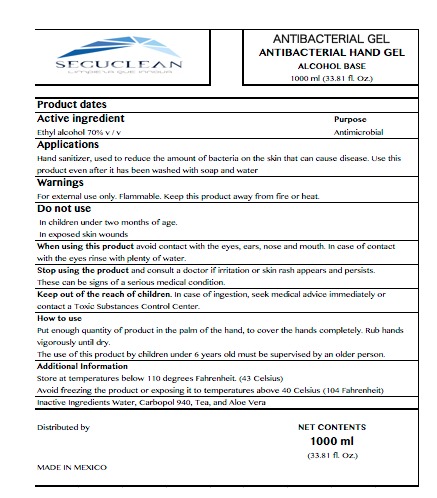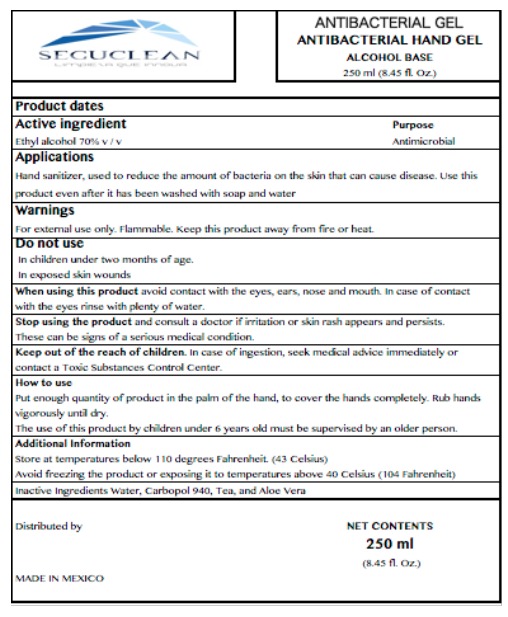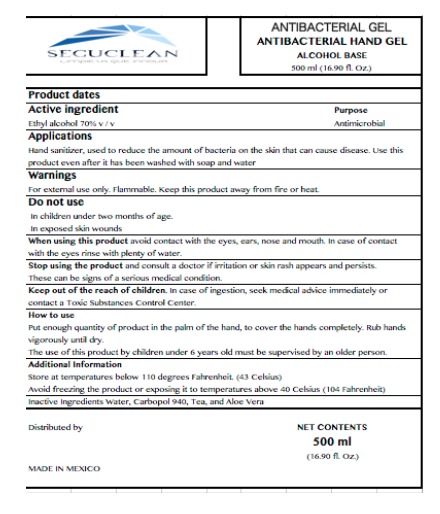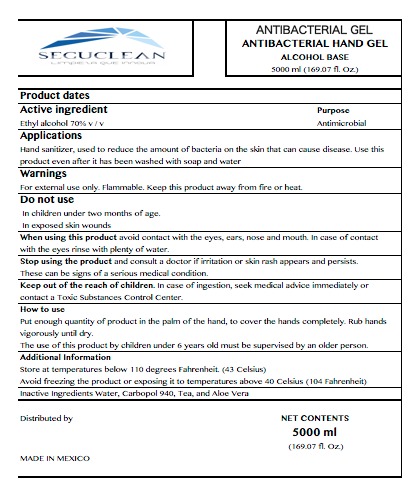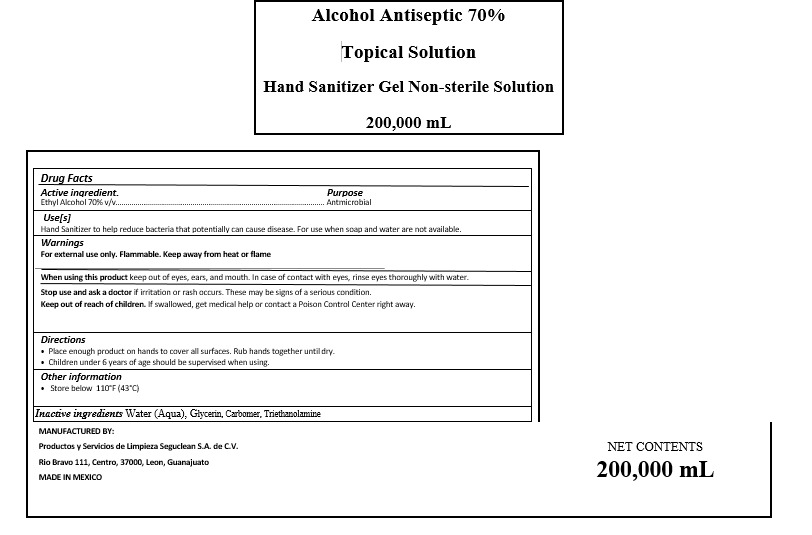 DRUG LABEL: SEGUCLEAN
NDC: 79594-2000 | Form: GEL
Manufacturer: Productos y Servicios de Limpieza Seguclean S.A. de C.V.
Category: otc | Type: HUMAN OTC DRUG LABEL
Date: 20200721

ACTIVE INGREDIENTS: ALCOHOL 0.55 mL/1 mL
INACTIVE INGREDIENTS: CARBOMER 940 0.004 mL/1 mL; WATER 0.436 mL/1 mL; TRIETHANOLAMINE CAPROYL GLUTAMATE 0.007 mL/1 mL; ALOE VERA LEAF 0.003 mL/1 mL

HAND SANITIZER GEL SEGUCLEAN

ACTIVE INGREDIENTS

Active ingredient Ethyl Alcohol 70% v/v

PURPOSE

Purpose Antmicrobial

DOSAGE AND ADMINISTRATION

Directions

Place enough product on hands to cover all surfaces. Rub hands together until dry.

INDICATIONS AND USAGE

Use[s]

Hand Sanitizer to help reduce bacteria that potentially can cause disease. For use when soap and water are not available.

WARNINGS

For external use only. Flammable. Keep away from heat or flame

WARNINGS AND PRECAUTIONS

When using this product keep out of eyes, ears, and mouth. In case of contact with eyes, rinse eyes thoroughly with water.

Children under 6 years of age should be supervised when using.

STOP USE SECTIONS

Stop use and ask a doctor if irritation or rash occurs. These may be signs of a serious condition.

Keep out of reach of children. If swallowed, get medical help or contact a Poison Control Center right away.

INACTIVE INGREDIENTS

Inactive ingredients Water (Aqua), Glycerin, Carbomer, Triethanolamine